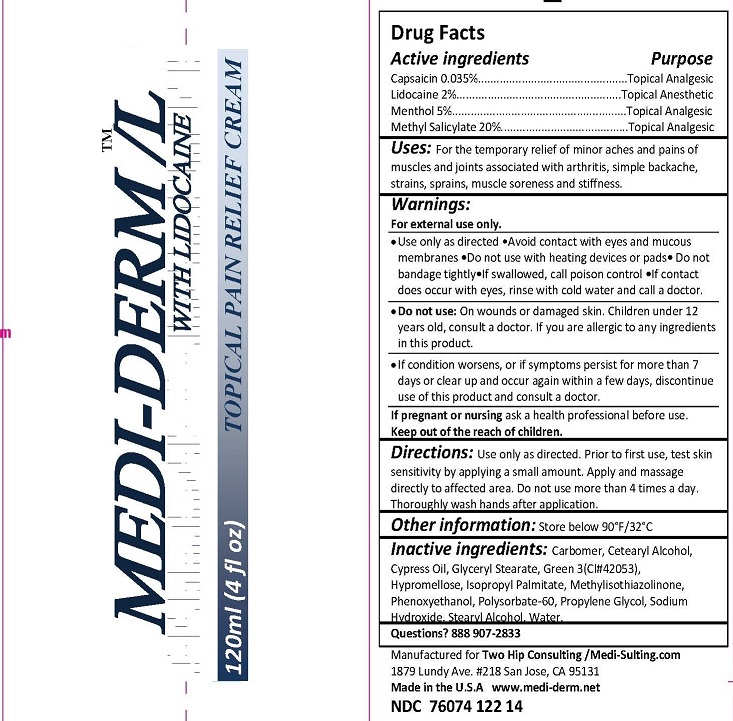 DRUG LABEL: MEDI-SULTING TOPICAL PAIN RELIEF
NDC: 76074-122 | Form: CREAM
Manufacturer: Two Hip Consulting, LLC
Category: otc | Type: HUMAN OTC DRUG LABEL
Date: 20190206

ACTIVE INGREDIENTS: METHYL SALICYLATE 20 g/100 mL; MENTHOL 5 g/100 mL; CAPSAICIN .0355 g/100 mL; LIDOCAINE 4 g/100 mL
INACTIVE INGREDIENTS: CARBOMER HOMOPOLYMER TYPE B (ALLYL SUCROSE CROSSLINKED); CETOSTEARYL ALCOHOL; GLYCERYL MONOSTEARATE; FD&C GREEN NO. 3; HYPROMELLOSE 2208 (100000 MPA.S); ISOPROPYL PALMITATE; METHYLISOTHIAZOLINONE; PHENOXYETHANOL; POLYSORBATE 60; PROPYLENE GLYCOL; SODIUM HYDROXIDE; STEARYL ALCOHOL; WATER

ACTIVE INGREDIENT

CAPSAICIN 0.035%

LIDOCAINE 2%

MENTHOL 5%

METHYL SALICYLATE 20%

PURPOSE

TOPICAL ANALGESIC

INDICATIONS AND USAGE

USES: FOR THE TEMPORARY RELIEF OF MINOR ACHES AND PAINS OF MUSCLES AND JOINTS ASSOCIATED WITH ARTHRITIS, SIMPLE BACKACHE, STRAINS, SPRAINS, MUSCLE SORENESS AND STIFFNESS.

WARNINGS

For external use only. Use only as directed. Avoid contact with eyes and mucous membranes. Do not use with heating devices or pads. Do not cover or bandage tightly. If swallowed, call poison control. If contact does occur with eyes rinse with cold water and call a doctor.

DO NOT USE: ON WOUNDS OR DAMAGED SKIN. CHILDREN UNDER 12 YEARS OLD, CONSULT A DOCTOR. IF YOU ARE ALLERGIC TO ANY INGREDIENTS IN THIS PRODUCT.

DOSAGE AND ADMINISTRATION

Directions: Use only as directed. Prior to first use, test skin sensitivity by applying a small amount. Apply and massage directly to affected area. Do not use more than 4 times a day. Thoroughly wash hands after application.

INACTIVE INGREDIENT

Inactive Ingredients: Carbomer, Cetearyl Alcohol, Cypress Oil, Glyceryl Stearate, Green 3 (CI# 42053), Hypromellose, Isopropyl Palmitate, Methylisothiazolinone, Phenoxyethanol, Polysorbate-60, Propylene Glycol, Sodium Hydroxide, Stearyl Alcohol, Water.

OTHER INFORMATION: STORE BELOW 90°F/32°C

QUESTIONS? 888 907-2833

ASK DOCTOR

IF CONDITION WORSENS, OR IF SYMPTOMS PERSIST FOR MORE THAN 7 DAYS OR CLEAR UP AND OCCUR AGAIN WITHIN A FEW DAYS, DISCONTINUE USE OF THIS PRODUCT AND CONSULT A DOCTOR.

PREGNANCY

IF PREGNANT OR NURSING ASK A HEALTH PROFESSIONAL BEFORE USE.

KEEP OUT OF REACH OF CHILDREN.